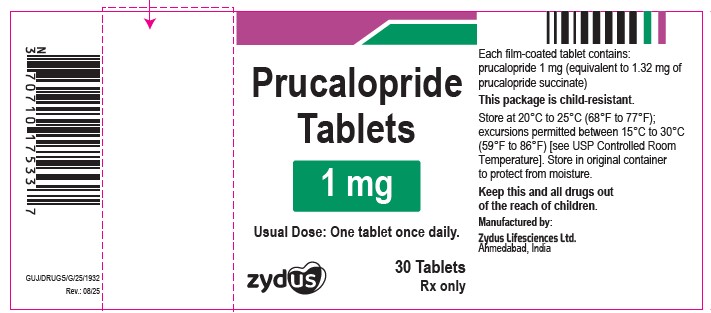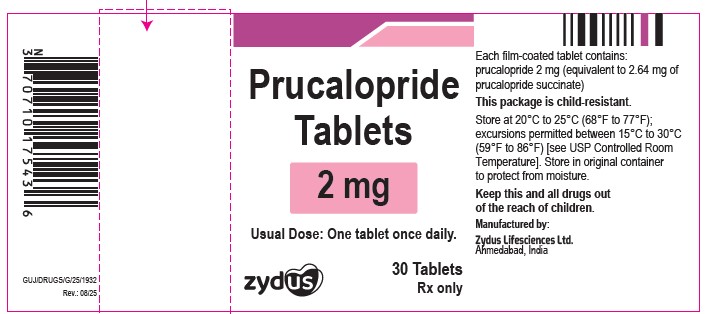 DRUG LABEL: prucalopride
NDC: 70771-1899 | Form: TABLET, FILM COATED
Manufacturer: Zydus Lifesciences Limited
Category: prescription | Type: HUMAN PRESCRIPTION DRUG LABEL
Date: 20260130

ACTIVE INGREDIENTS: PRUCALOPRIDE SUCCINATE 1 mg/1 1
INACTIVE INGREDIENTS: HYPROMELLOSE 2910 (3 MPA.S); MAGNESIUM STEARATE; MICROCRYSTALLINE CELLULOSE 101; POLYETHYLENE GLYCOL, UNSPECIFIED; SILICON DIOXIDE; STARCH, CORN; TITANIUM DIOXIDE; TRIACETIN

PRUCALOPRIDE tablets, for oral use

PACKAGE LABEL.PRINCIPAL DISPLAY PANEL

NDC 70771-1899-3

Prucalopride Tablets

1 mg tablet

30 Tablets

Rx only

NDC 70771-1900-3

Prucalopride Tablets

2 mg tablet

30 Tablets

Rx only